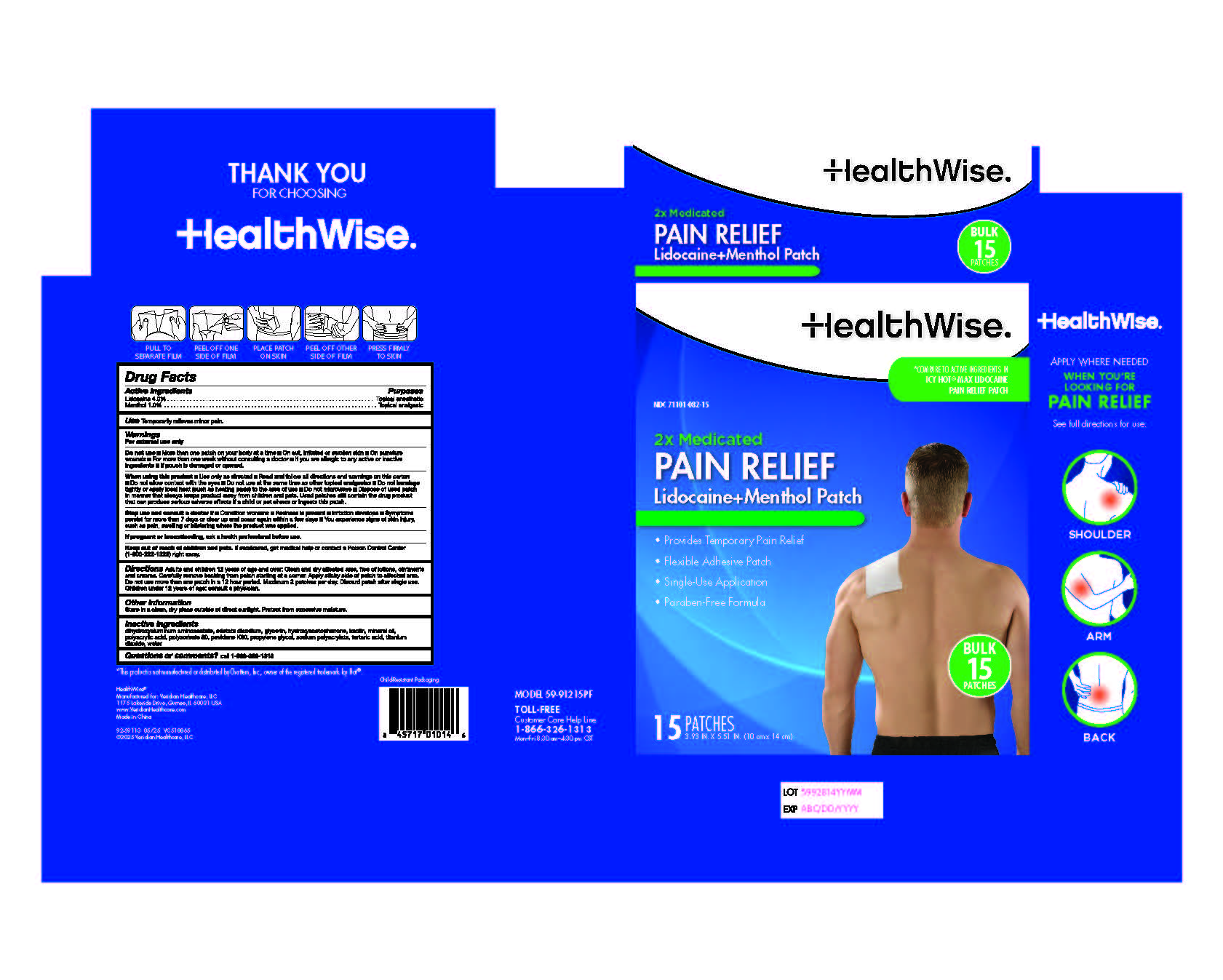 DRUG LABEL: HealthWise Lidocaine and Menthol
NDC: 71101-082 | Form: PATCH
Manufacturer: Veridian Healthcare
Category: otc | Type: HUMAN OTC DRUG LABEL
Date: 20250604

ACTIVE INGREDIENTS: LIDOCAINE 4 g/100 g; MENTHOL 1 g/100 g
INACTIVE INGREDIENTS: MINERAL OIL; DIHYDROXYALUMINUM AMINOACETATE ANHYDROUS; KAOLIN; GLYCERIN; EDETATE DISODIUM; POLYACRYLIC ACID (250000 MW); POLYSORBATE 80; PROPYLENE GLYCOL; HYDROXYACETOPHENONE; SODIUM POLYACRYLATE (2500000 MW); TARTARIC ACID; TITANIUM DIOXIDE; WATER; POVIDONE K90

HealthWise Lidocaine + Menthol Patch

Active ingredients

Lidocaine 4%

Menthol 1%

Purposes

Topical anesthetic

Topical analgesic

Use

for the temporary relief minor pain

Warnings

For external use only

Do not use

■ more than 1 patch on your body at a time

■ on a cut, irritated, or swollen skin

■ on puncture wounds

■ For more than one week without consulting a doctor.

■ if you are allergic to any active or inactive ingredients

■ if pouch is damaged or opened

When using this product

■ use only as directed

■ read and follow all directions and warnings on this carton

■ do not allow contact with the eyes

■ do not use at the same time as other topical analgesics

■ do not bandage tightly or apply local heat (such as heating pads) to the area of use

■do not microwave

■ dispose of used patch in manner that always keeps product away from children and pets. Used patches still

contain the drug product that can produce serious adverse effects if a child or pet chews or ingests this patch.

Stop use and ask a doctor if

■ condition worsens

■ redness is present

■ irritation develops

■ symptoms persist for more than 7 days or clear up and occur again within a few days

■ you experience signs of skin injury, such pain, swelling, or blistering where the product was applied

If pregnant or breast-feeding,

ask a health professional before use.

Keep out of reach of children and pets.

If swallowed, get medical help or contact a Poison Control Center 800-222-1222 right away.

Directions

adults and children 12 years of age and over:

■ clean and dry affected area, free of lotions, oitments and creams.

■ Carefully remove backing from patch starting at a corner

■ Apply sticky side of patch to affected area

■ Maximum 2 patches per day.

■ Discard patch after single use

children under 12 years of age: consult a physician

Inactive ingredients

dihydroxyaluminum aminoacetate, edetate disodium, glycerin, hydroxyacetophenone, kaolin, mineral oil, polyacrylic acid, polysorbate 80, povidone K90, propylene glycol, sodium polyacrylate, tartaric acid, titanium dioxide, water